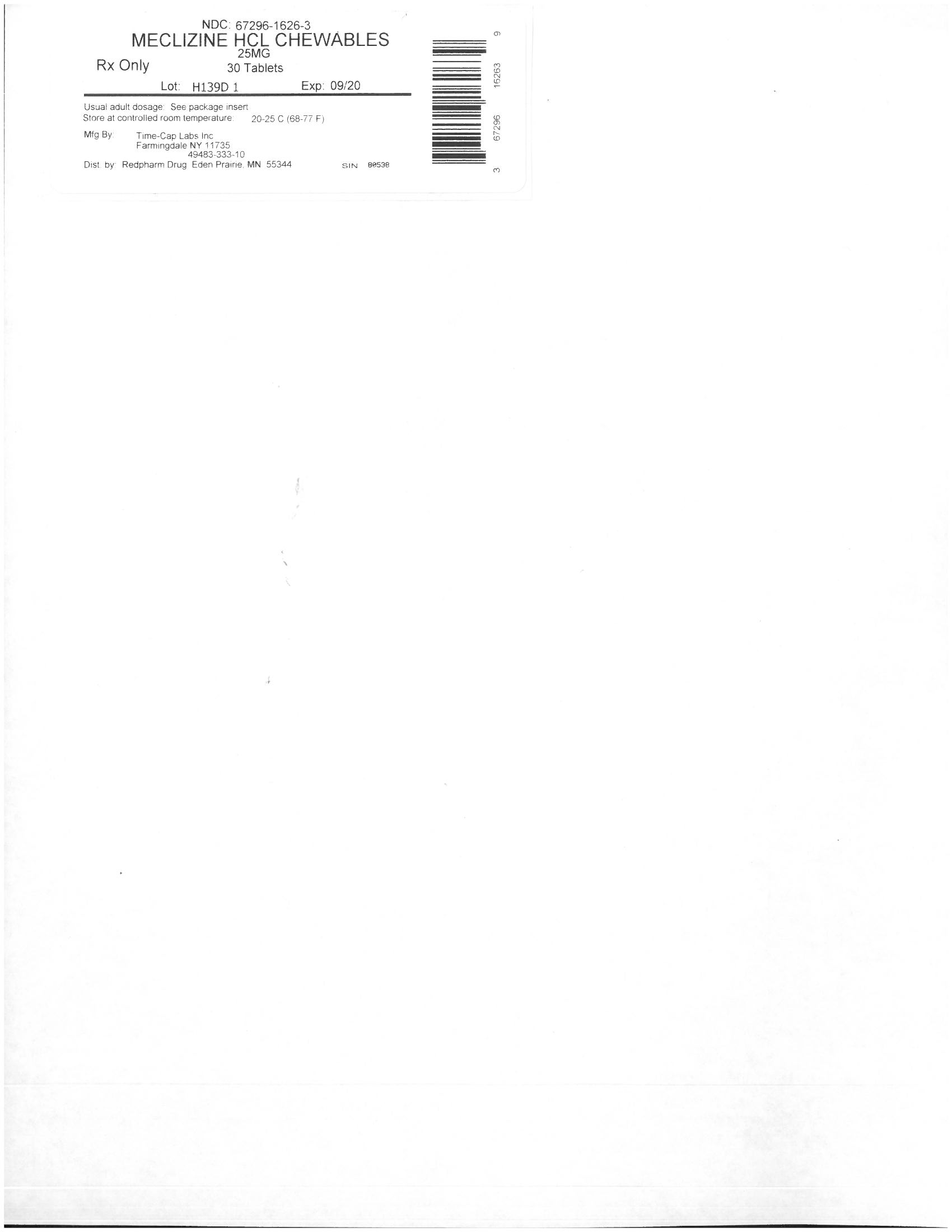 DRUG LABEL: Motion-Time
NDC: 67296-1626 | Form: TABLET, CHEWABLE
Manufacturer: RedPharm Drug, Inc.
Category: otc | Type: HUMAN OTC DRUG LABEL
Date: 20210113

ACTIVE INGREDIENTS: MECLIZINE HYDROCHLORIDE 25 mg/25 1
INACTIVE INGREDIENTS: ANHYDROUS LACTOSE; CROSPOVIDONE; DEXTROSE; FD&C RED NO. 40; MAGNESIUM STEARATE; CELLULOSE, MICROCRYSTALLINE; MODIFIED CORN STARCH (1-OCTENYL SUCCINIC ANHYDRIDE); PROPYLENE GLYCOL; RASPBERRY; SILICON DIOXIDE; SACCHARIN SODIUM; STEARIC ACID; TALC; VANILLA

MECLIZINE 25MG

Active ingredient (in each tablet)

Meclizine HCl 25 mg

Purpose

Antiemetic

Uses

prevents and treats nausea, vomiting, or dizziness associated with motion sickness

Warnings

Do not give to children under 12 years of age unless directed by a doctor

ASK DOCTOR

Do not take unless directed by a doctor if you have

- trouble urinating due to an enlarged prostate gland
- glaucoma
- a breathing problem such as emphysema or chronic bronchitis

Do not take if you are

taking sedatives or tranquilizers, without first consulting your doctor

When using this product

- do not exceed recommended dosage
- drowsiness may occur
- avoid alcoholic drinks
- alcohol, sedatives, and tranquilizers may increase drowsiness
- be careful when driving a motor vehicle or operating machinery

If pregnant or breast-feeding,

ask a health professional before use.

Keep out of reach of children.

In case of overdose, get medical help or contact a Poison Control Center right away.

Directions

- dosage should be taken one hour before travel starts
- adults and children 12 years of age and over: take 1 to 2 tablets once daily or as directed by a doctor

Other information

- store at 25°C (77°F) excursions permitted between 15°-30°C (59°-86°F) in a dry place
- use by expiration date on package

Inactive ingredients

anhydrous lactose, colloidal silicon dioxide, crospovidone, dextrose, FD-C red 40 aluminum lake, magnesium stearate, microcrystalline cellulose, modified corn starch, propylene glycol, raspberry flavor, silicon dioxide, sodium saccharin, stearic acid, talc, vanilla flavor